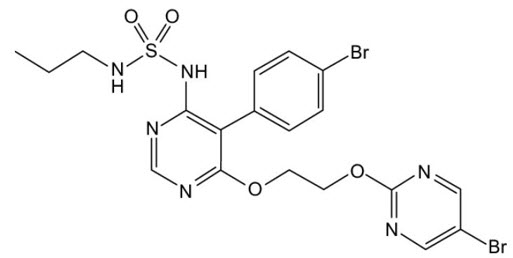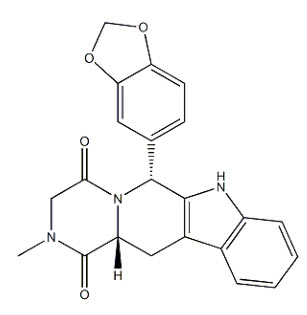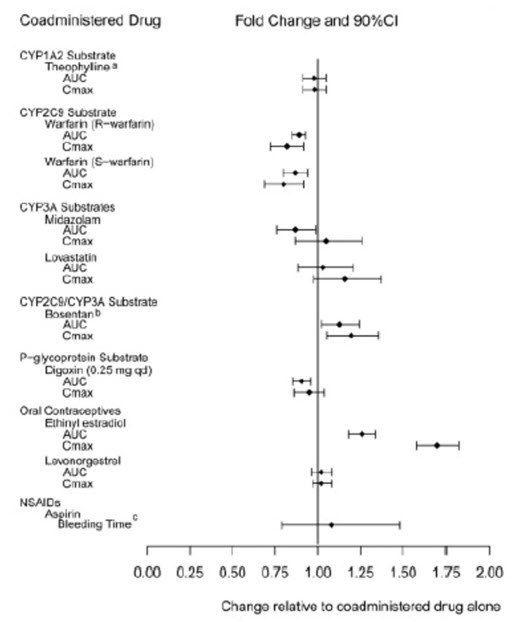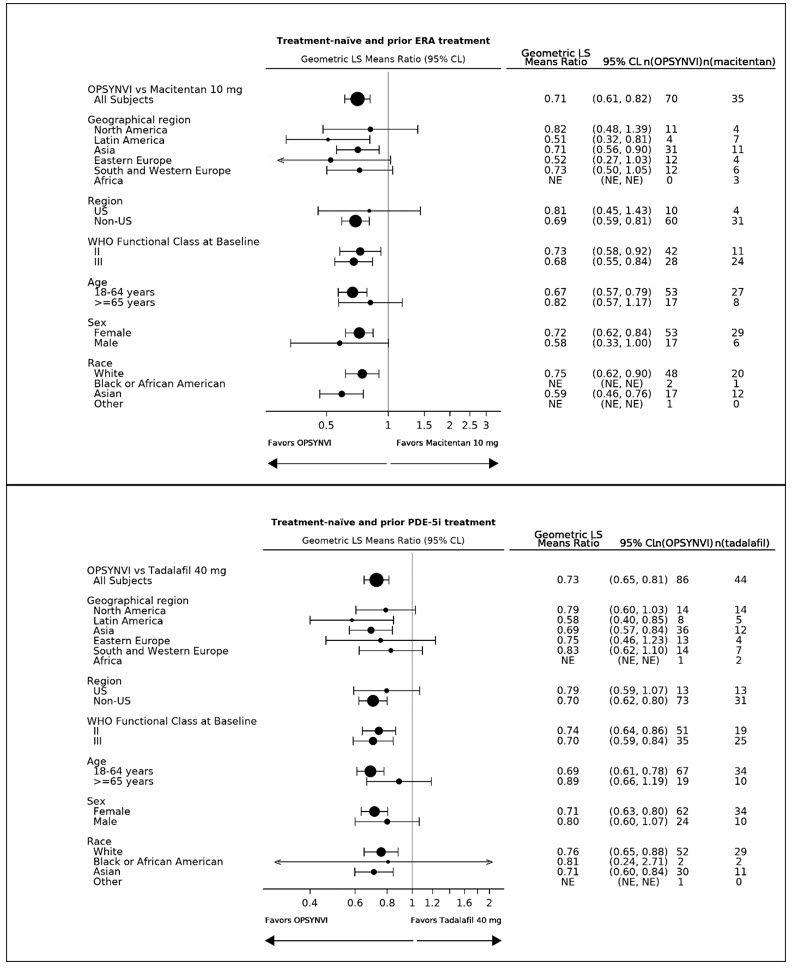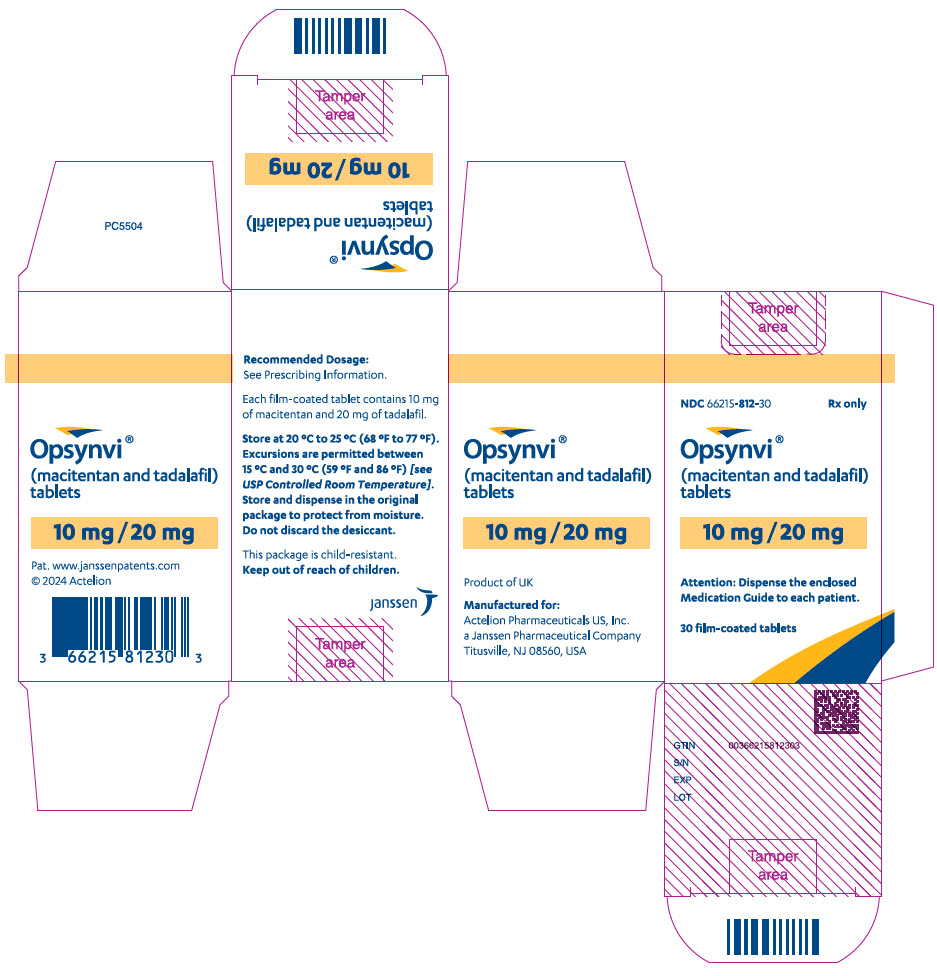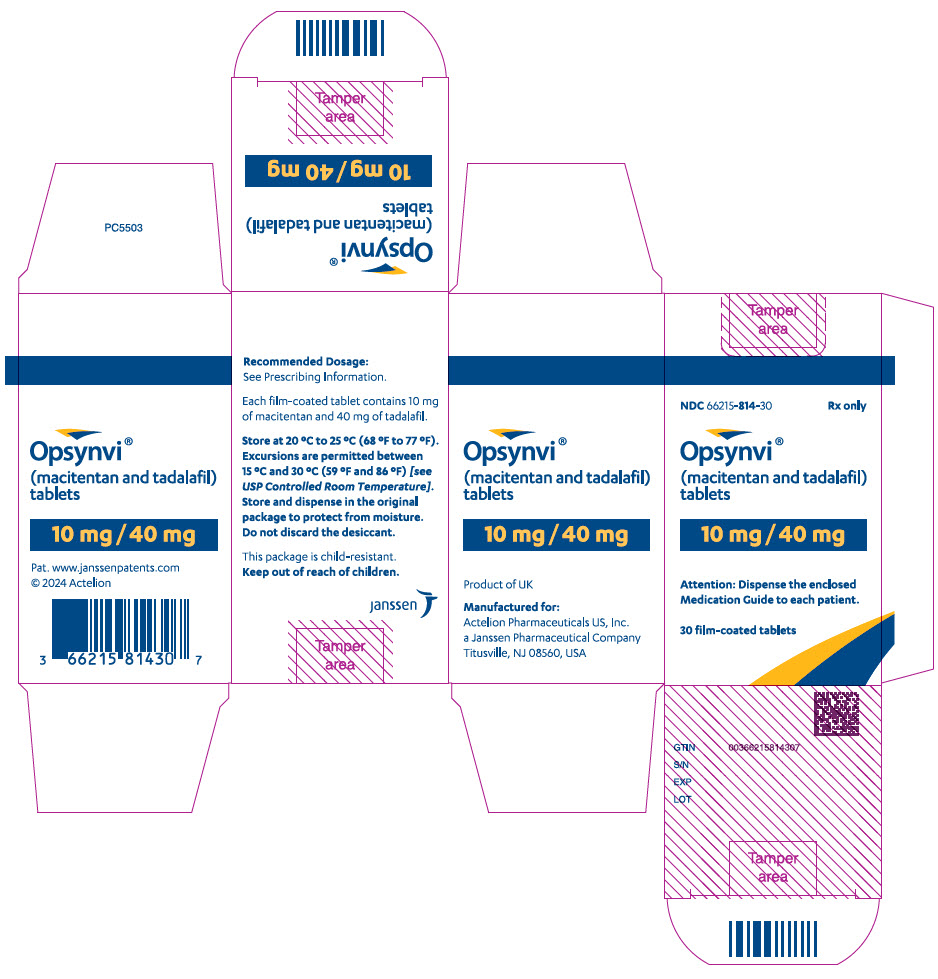 DRUG LABEL: OPSYNVI
NDC: 66215-814 | Form: TABLET, FILM COATED
Manufacturer: Actelion Pharmaceuticals US, Inc.
Category: prescription | Type: HUMAN PRESCRIPTION DRUG LABEL
Date: 20250411

ACTIVE INGREDIENTS: MACITENTAN 10 mg/1 1; TADALAFIL 40 mg/1 1
INACTIVE INGREDIENTS: HYDROXYPROPYL CELLULOSE, UNSPECIFIED; LOW-SUBSTITUTED HYDROXYPROPYL CELLULOSE, UNSPECIFIED; LACTOSE MONOHYDRATE; MAGNESIUM STEARATE; MICROCRYSTALLINE CELLULOSE; POLYSORBATE 80; POVIDONE K30; SODIUM STARCH GLYCOLATE TYPE A; SODIUM LAURYL SULFATE; HYPROMELLOSE, UNSPECIFIED; TALC; TITANIUM DIOXIDE; TRIACETIN

HIGHLIGHTS OF PRESCRIBING INFORMATION

These highlights do not include all the information needed to use OPSYNVI safely and effectively. See full prescribing information for OPSYNVI.
OPSYNVI®(macitentan and tadalafil) tablets, for oral use
Initial U.S. Approval: 2024

WARNING: EMBRYO-FETAL TOXICITY

See full prescribing information for complete boxed warning.

- Based on animal data, OPSYNVI may cause fetal harm if used during pregnancy (4.1, 5.1, 8.1).
- Females of reproductive potential: exclude pregnancy before start of treatment. Prevent pregnancy prior to initiation of treatment, during treatment and for one month after treatment by using effective methods of contraception (2.2, 8.3).
- When pregnancy is detected, discontinue OPSYNVI as soon as possible (5.1).

RECENT MAJOR CHANGES

Boxed Warning | 4/2025
Dosage and Administration (2.2) | 4/2025
Warnings and Precautions (5.1) | 4/2025
Warnings and Precautions (5.2) | Removal 4/2025

1 INDICATIONS AND USAGE

OPSYNVI is a combination of macitentan, an endothelin receptor antagonist (ERA), and tadalafil, a phosphodiesterase 5 (PDE5) inhibitor, indicated for chronic treatment of pulmonary arterial hypertension (PAH, WHO Group I) in adult patients of WHO functional class (FC) II–III. (1.1)

Individually, macitentan reduces the risk of clinical worsening events and hospitalization, and tadalafil improves exercise ability. (1.1, 14)

2 DOSAGE AND ADMINISTRATION

- One 10 mg/20 mg or 10 mg/40 mg tablet taken orally once daily with or without food. (2.1)

3 DOSAGE FORMS AND STRENGTHS

Film-coated tablets:

- Macitentan 10 mg and tadalafil 20 mg (3)
- Macitentan 10 mg and tadalafil 40 mg (3)

4 CONTRAINDICATIONS

- Pregnancy (4.1)
- Hypersensitivity (4.2)
- Concomitant Organic Nitrates (4.3)
- Concomitant Guanylate Cyclase (GC) Stimulators (4.4)

5 WARNINGS AND PRECAUTIONS

- Hepatotoxicity: ERAs cause hepatotoxicity and liver failure. Obtain baseline liver enzymes and monitor as clinically indicated. (5.2)
- Hypotension: Vasodilatory effects may cause hypotension in susceptible patients. (5.3)
- Hemoglobin decrease. (5.4)
- Worsening Pulmonary Veno-Occlusive Disease: If pulmonary edema is confirmed, discontinue treatment. (5.5)
- Visual Loss: Sudden loss of vision could be a sign of non-arteritic ischemic optic neuropathy (NAION) and may be permanent. (5.6)
- Hearing Impairment: Cases of sudden decrease or loss of hearing have been reported in patients taking tadalafil. (5.7)
- Fluid Retention: Fluid retention may require intervention. (5.8)
- Combination with Other PDE5 Inhibitors: Avoid use with other PDE5 inhibitors. (5.9)
- Decreased Sperm Count: Decreases in sperm count have been observed in patients taking ERAs. (5.10)
- Prolonged Erection: Advise patients to seek emergency treatment if an erection lasts greater than 4 hours. (5.11)

6 ADVERSE REACTIONS

Most common adverse reactions (≥10%) are edema/fluid retention, anemia, and headache/migraine. (6.1)

To report SUSPECTED ADVERSE REACTIONS, contact Janssen at 1-800-526-7736 (1-800-JANSSEN) or FDA at 1-800-FDA-1088 or www.fda.gov/medwatch.

7 DRUG INTERACTIONS

- Strong CYP3A4 Inducers/Inhibitors: Avoid concomitant use (7.2, 7.3)
- Moderate Dual or Combined CYP3A4 and CYP2C9 Inhibitors: Avoid concomitant use (7.4)

8 USE IN SPECIFIC POPULATIONS

- Lactation: Advise not to breastfeed (8.2)
- Renal Impairment: Avoid use in patients with creatinine clearance 15–29 mL/min (8.6)
- Hepatic Impairment: Do not initiate in patients with severe hepatic impairment (8.7)

FULL PRESCRIBING INFORMATION

WARNING: EMBRYO-FETAL TOXICITY

OPSYNVI is contraindicated for use during pregnancy because it may cause fetal harm based on animal data [see Contraindications (4.1), Warnings and Precautions (5.1), Use in Specific Populations (8.1)].

Therefore, for females of reproductive potential, exclude pregnancy before the start of treatment with OPSYNVI. Advise use of effective contraception before the initiation of treatment, during treatment, and for one month after stopping treatment with OPSYNVI [see Dosage and Administration (2.2), Use in Specific Populations (8.3)]. When pregnancy is detected, discontinue OPSYNVI as soon as possible [see Warnings and Precautions (5.1)] .

1 INDICATIONS AND USAGE

1.1 Pulmonary Arterial Hypertension

OPSYNVI is the combination of macitentan and tadalafil indicated for the chronic treatment of adults with pulmonary arterial hypertension (PAH, WHO Group I and WHO Functional Class (FC) II–III).

Individually, macitentan reduces the risk of clinical worsening events and hospitalization, and tadalafil improves exercise ability [see Clinical Studies (14.1)] .

2 DOSAGE AND ADMINISTRATION

2.1 Recommended Dosage

OPSYNVI is taken orally once daily with or without food. Swallow the tablets whole, with water. Do not cut, crush, or chew tablets. If the patient misses a dose of OPSYNVI, tell the patient to take it as soon as possible and then take the next dose at the regularly scheduled time. Tell the patient not to take two doses at the same time if a dose has been missed.

For patients who are treatment-naïve to any PAH specific therapy or transitioning from ERA monotherapy

The recommended starting dose of OPSYNVI is one 10 mg/20 mg tablet taken orally once daily with or without food for one week. If tolerated, up titrate OPSYNVI to one 10 mg/40 mg tablet taken orally once daily with or without food as the maintenance dose.

For patients transitioning from PDE5 inhibitor monotherapy or PDE5 inhibitor and ERA therapy in combination

The recommended dose of OPSYNVI is one 10 mg/40 mg tablet taken orally once daily.

2.2 Pregnancy Testing in Females of Reproductive Potential

Exclude pregnancy before initiating treatment with OPSYNVI in females of reproductive potential [see Boxed Warning, Contraindications (4.1), Warnings and Precautions (5.1), and Use in Specific Populations (8.3)].

3 DOSAGE FORMS AND STRENGTHS

OPSYNVI is available as:

10 mg/20 mg | Pink | Oblong | Film-coated | "1020" on one side and "MT" on the other side
10 mg/40 mg | White to almost-white | Oblong | Film-coated | "1040" on one side and "MT" on the other side

4 CONTRAINDICATIONS

4.1 Pregnancy

OPSYNVI may cause fetal harm when administered to a pregnant woman. OPSYNVI is contraindicated in females who are pregnant. Macitentan was consistently shown to have teratogenic effects when administered to animals. If OPSYNVI is used during pregnancy, advise the patient of the potential risk to a fetus [see Warnings and Precautions (5.1)and Use in Specific Populations (8.1)] .

4.2 Hypersensitivity

OPSYNVI is contraindicated in patients with a history of a hypersensitivity reaction to macitentan, tadalafil, or any component of the product. Hypersensitivity reactions have been reported. Stevens-Johnson syndrome and exfoliative dermatitis have been reported with tadalafil [see Adverse Reactions (6.2)].

4.3 Concomitant Organic Nitrates

OPSYNVI is contraindicated in patients who are using any form of organic nitrate, either regularly or intermittently. Do not use nitrates within 48 hours of the last dose of OPSYNVI. Tadalafil potentiates the hypotensive effect of nitrates. This potentiation is thought to result from the combined effects of nitrates and tadalafil on the nitric oxide/cGMP pathway [see Clinical Pharmacology (12.2)].

4.4 Concomitant Guanylate Cyclase (GC) Stimulators

Coadministration of GC stimulators such as riociguat with OPSYNVI is contraindicated. Tadalafil may potentiate the hypotensive effects of GC stimulators.

5 WARNINGS AND PRECAUTIONS

5.1 Embryo-fetal Toxicity

Based on data from animal reproduction studies, OPSYNVI may cause fetal harm when administered to a pregnant patient and is contraindicated during pregnancy. The available human data for ERAs do not establish the presence or absence of major birth defects related to the use of OPSYNVI. Advise patients who can become pregnant of the potential risk to a fetus. Obtain a pregnancy test prior to initiation of therapy with OPSYNVI. Advise patients who can become pregnant to use effective contraceptive methods prior to initiation of treatment, during treatment, and for one month after discontinuation of treatment with OPSYNVI. When pregnancy is detected, discontinue use as soon as possible [see Dosage and Administration (2.2), Contraindications (4.1), and Use in Specific Populations (8.1, 8.3)].

5.2 Hepatotoxicity

ERAs have caused elevations of aminotransferases, hepatotoxicity, and liver failure.

The incidence of elevated aminotransferases in the double-blind and combined double-blind (DB)/open-label (OL) arms of the study of OPSYNVI in PAH are shown in Table 1.

Table 1: Incidence of Elevated Aminotransferases in the A DUE Study
 | OPSYNVI DB (N=107) | OPSYNVI DB/OL (N=185)
≥3 × ULN | 1.0% | 3.4%
≥8 × ULN | 1.0% | 1.1%

The overall incidence of treatment discontinuations for hepatic adverse events in the double-blind and combined double-blind/open-label arms study of OPSYNVI in PAH data were 0.9% and 2.2% respectively.

The incidence of elevated aminotransferases in the study of OPSUMIT (macitentan) in PAH is shown in Table 2.

Table 2: Incidence of Elevated Aminotransferases in the SERAPHIN Study
 | OPSUMIT 10 mg (N=242) | Placebo (N=249)
>3 × ULN | 3.4% | 4.5%
>8 × ULN | 2.1% | 0.4%

In the placebo-controlled study of OPSUMIT, discontinuations for hepatic adverse events were 3.3% in the OPSUMIT 10 mg group vs. 1.6% for placebo.

Obtain liver enzyme tests prior to initiation of OPSYNVI and repeat during treatment as clinically indicated.

Advise patients to report symptoms suggesting hepatic injury (nausea, vomiting, right upper quadrant pain, fatigue, anorexia, jaundice, dark urine, fever, or itching). If clinically relevant aminotransferase elevations occur, or if elevations are accompanied by an increase in bilirubin >2 × ULN, or by clinical symptoms of hepatotoxicity, discontinue OPSYNVI. Consider re-initiation of OPSYNVI when hepatic enzyme levels normalize in patients who have not experienced clinical symptoms of hepatotoxicity.

Do not initiate OPSYNVI in patients with elevated aminotransferases (> 3 × upper limit of normal [ULN]) at baseline. Patients with severe hepatic cirrhosis (Child-Pugh Class C) have not been studied, and, therefore, avoid use of OPSYNVI.

5.3 Hypotension

OPSYNVI tablets have vasodilatory properties that may result in transient decreases in blood pressure. Prior to prescribing OPSYNVI tablets, carefully consider whether patients with underlying cardiovascular disease could be affected adversely by such vasodilatory effects. Patients with pre-existing hypotension, with autonomic dysfunction, with left ventricular outflow obstruction, may be particularly sensitive to the actions of vasodilators [see Clinical Pharmacology (12.2)].

5.4 Hemoglobin Decrease

Decreases in hemoglobin concentration and hematocrit have occurred following administration of other ERAs and were observed in clinical studies with OPSYNVI and OPSUMIT. These decreases occurred early and stabilized thereafter.

In the placebo-controlled study of OPSUMIT in PAH, OPSUMIT 10 mg caused a mean decrease in hemoglobin from baseline to up to 18 months of about 1.0 g/dL compared to no change in the placebo group. A decrease in hemoglobin to below 10.0 g/dL was reported in 8.7% of the OPSUMIT 10 mg group and in 3.4% of the placebo group. Similar results were observed in the trial with OPSYNVI.

Decreases in hemoglobin seldom require transfusion. Initiation of OPSYNVI is not recommended in patients with severe anemia. Measure hemoglobin prior to initiation of treatment and repeat during treatment as clinically indicated [see Adverse Reactions (6.1)].

5.5 Worsening Pulmonary Veno-Occlusive Disease (PVOD)

Pulmonary vasodilators may significantly worsen the cardiovascular status of patients with pulmonary veno-occlusive disease (PVOD). Since there are no clinical data on administration of OPSYNVI tablets to patients with veno-occlusive disease, administration of OPSYNVI tablets to such patients is not recommended. Should signs of pulmonary edema occur when OPSYNVI tablets are administered, the possibility of associated PVOD should be considered. If confirmed, discontinue OPSYNVI.

5.6 Visual Loss

Non–arteritic anterior ischemic optic neuropathy (NAION), a cause of decreased vision, including permanent loss of vision, has been reported postmarketing in temporal association with the use of PDE5 inhibitors, including tadalafil. Most, but not all, of these patients had underlying anatomic or vascular risk factors for development of NAION, including: low cup to disc ratio ("crowded disc"), age over 50, diabetes, hypertension, coronary artery disease, hyperlipidemia, and smoking. Based on published literature, the annual incidence of NAION is 2.5–11.8 cases per 100,000 in males aged greater than or equal to 50 in the general population. Other risk factors for NAION, such as the presence of "crowded" optic disc, may have contributed to the occurrence of NAION.

Patients with known hereditary degenerative retinal disorders, including retinitis pigmentosa, were not included in the clinical trials, and use of OPSYNVI in these patients is not recommended.

5.7 Hearing Impairment

Cases of sudden decrease or loss of hearing, which may be accompanied by tinnitus and dizziness, have been reported in patients taking tadalafil. It is not possible to determine whether these events are related directly to the use of PDE5 inhibitors or to other factors.

5.8 Fluid Retention

Peripheral edema and fluid retention are known clinical consequences of PAH and known effects of ERAs and heart failure has been reported in patients taking OPSYNVI. In the active-controlled and combined double-blind/open-label arms of the study of OPSYNVI in PAH, the incidence of peripheral edema/fluid retention was 20.6% in the active-controlled and 17.3% in the double-blind/open-label arm [see Adverse Reactions (6.1)] . In the placebo-controlled study of OPSUMIT in PAH, the incidence of edema was 21.9% in the OPSUMIT 10 mg group and 20.5% in the placebo group.

Patients with underlying left ventricular dysfunction may be at particular risk for developing significant fluid retention after initiation of ERA treatment. In a small study of OPSUMIT in patients with pulmonary hypertension because of left ventricular dysfunction, more patients in the OPSUMIT group developed significant fluid retention and had more hospitalizations because of worsening heart failure compared to those randomized to placebo. Postmarketing cases of edema and fluid retention occurring within weeks of starting OPSUMIT, some requiring intervention with a diuretic or hospitalization for decompensated heart failure, have been reported .

Monitor for signs of fluid retention after OPSYNVI initiation. If clinically significant fluid retention develops, evaluate the patient to determine the cause, such as OPSYNVI or underlying heart failure, and the possible need to discontinue OPSYNVI.

5.9 Combination with Other PDE5 Inhibitors

Tadalafil is also indicated for erectile dysfunction. The safety and efficacy of taking tadalafil tablets together with another PDE5 inhibitors or other treatments for erectile dysfunction have not been studied. Instruct patients taking OPSYNVI tablets not to take other PDE5 inhibitors.

5.10 Decreased Sperm Count

Macitentan, like other ERAs, may have an adverse effect on spermatogenesis. Counsel men about potential effects on fertility [see Use in Specific Populations (8.3)and Nonclinical Toxicology (13.1)].

5.11 Prolonged Erection

There have been reports of prolonged erections greater than 4 hours and priapism (painful erections greater than 6 hours in duration) for PDE5 inhibitors like tadalafil. Patients with conditions that might predispose them to priapism (such as sickle cell anemia, multiple myeloma, or leukemia), or in patients with anatomical deformation of the penis (such as angulation, cavernosal fibrosis, or Peyronie's disease) are at an increased risk. Priapism, if not treated promptly, can result in irreversible damage to the erectile tissue. Patients who have an erection lasting greater than 4 hours, whether painful or not, should seek emergency medical attention.

6 ADVERSE REACTIONS

Clinically significant adverse reactions that appear in other sections of the labeling include:

- Hypersensitivity [see Contraindications (4.2)]
- Embryo-fetal Toxicity [see Warnings and Precautions (5.1)]
- Hepatotoxicity [see Warnings and Precautions (5.2)]
- Hypotension [see Warnings and Precautions (5.3)]
- Decrease in Hemoglobin [see Warnings and Precautions (5.4)]
- Visual Loss [see Warnings and Precautions (5.6)and Patient Counseling Information (17)]
- Hearing loss [see Warnings and Precautions (5.7)]
- Fluid Retention [see Warnings and Precautions (5.8)]
- Prolonged Erection [see Warnings and Precautions (5.11)]

6.1 Clinical Trials Experience

Because clinical trials are conducted under widely varying conditions, adverse reaction rates observed in the clinical trials of a drug cannot be directly compared to rates in the clinical trials of another drug and may not reflect the rates observed in practice.

The overall safety profile of OPSYNVI is based on data from a double-blind, active-controlled, phase 3 clinical study (A DUE) and an open-label extension study, in patients with PAH [see Clinical Studies (14)] . In the double-blind portion of the study, a total of 107 patients were treated with OPSYNVI 10 mg/40 mg, 35 patients were treated with 10 mg macitentan monotherapy, and 44 patients were treated with 40 mg tadalafil monotherapy. The duration of exposure to OPSYNVI during the double-blind portion was 16 weeks.

The most common adverse reactions (occurring in ≥ 10% of the OPSYNVI-treated patients) from the double-blind study data were edema/fluid retention (21%), anemia (19%), and headache/migraine (18%). The incidence of treatment discontinuations due to adverse events among patients receiving OPSYNVI in the double-blind phase of the study was 8%. The most frequent adverse reactions leading to discontinuation were anemia and hemoglobin decreased (2% grouped) and peripheral edema and peripheral swelling (2% grouped). Table 3 presents adverse reactions seen in patients treated for 16 weeks during the double-blind portion of A DUE.

Table 3: Adverse Reactions Occurring in 3% or More of Patients Treated with OPSYNVI During the 16-week Double-blind Study Portion of A DUE
Adverse Reaction | OPSYNVI N=107 % | Macitentan Monotherapy N=35 % | Tadalafil Monotherapy N=44 %
Edema/fluid retention | 21 | 14 | 16
Anemia | 19 | 3 | 2
Headache | 18 | 17 | 14
Abdominal pain | 7 | 3 | 14
Hypotension | 7 | 0 | 0
Myalgia | 6 | 0 | 5
Nasopharyngitis | 6 | 3 | 0
Nausea | 6 | 0 | 7
Increased uterine bleeding | 5 | 0 | 0
Back pain | 5 | 3 | 9
Flushing | 4 | 6 | 0
Vomiting | 4 | 0 | 5
Palpitations | 4 | 3 | 5
Pain in extremity | 3 | 0 | 7
Epistaxis | 3 | 0 | 0

One-hundred eighty-five patients received OPSYNVI in the double-blind or open-label phase of the study. The median exposure to OPSYNVI during the combined double-blind/open-label extension was 59.9 weeks with a mean exposure of 63.2 weeks. Adverse reactions from the combined double-blind/open-label study data were similar to those observed in the double-blind study.

The following adverse reactions have been reported during clinical trials with the individual components of OPSYNVI but were not observed in 3% or more of subjects treated with OPSYNVI in the A DUE clinical trial:

Macitentan: bronchitis, pharyngitis, transaminases increased, influenza, urinary tract infection.

Tadalafil: lower respiratory tract infection, prolonged erections, gastroesophageal reflux disease, vision blurred, tinnitus, swelling face, chest pain.

6.2 Postmarketing Experience

Additional adverse reactions have been identified during post-approval use of tadalafil. Because these reactions are reported voluntarily from a population of uncertain size, it is generally not possible to reliably estimate their frequency or establish a causal relationship to drug exposure.

Macitentan: liver injury, symptomatic hypotension, hypersensitivity reactions (angioedema, pruritus, and rash).

Tadalafil: Cardiovascular and cerebrovascular events including myocardial infarction, sudden cardiac death, stroke, and tachycardia; Nervous system events including, seizure, transient amnesia; Hypersensitivity reactions including urticaria, Stevens-Johnson syndrome, and exfoliative dermatitis; visual field defect, NAION, retinal vascular occlusion; sudden hearing loss, priapism.

7 DRUG INTERACTIONS

7.1 Nitrates

Administration of nitrates within 48 hours after the last dose of OPSYNVI is contraindicated [see Contraindications (4.3)] .

7.2 Strong CYP3A4 Inducers

Strong inducers of CYP3A4 such as rifampin significantly reduce macitentan exposure. Use of OPSYNVI with strong CYP3A4 inducers should be avoided [see Clinical Pharmacology (12.3)].

7.3 Strong CYP3A4 Inhibitors

Concomitant use of strong CYP3A4 inhibitors like ketoconazole increase exposure to both macitentan and tadalafil. Avoid concomitant use of OPSYNVI with strong CYP3A4 inhibitors such as ritonavir, ketoconazole and itraconazole. Use other PAH treatment options when strong CYP3A4 inhibitors are needed [see Clinical Pharmacology (12.3)].

7.4 Moderate Dual or Combined CYP3A4 and CYP2C9 Inhibitors

Concomitant use of moderate dual inhibitors of CYP3A4 and CYP2C9 such as fluconazole is predicted to increase macitentan exposure approximately 4-fold. Avoid concomitant use of OPSYNVI with moderate dual inhibitors of CYP3A4 and CYP2C9 (such as fluconazole and amiodarone) [see Clinical Pharmacology (12.3)].

Concomitant treatment of both a moderate CYP3A4 inhibitor and moderate CYP2C9 inhibitor with OPSYNVI should also be avoided [see Clinical Pharmacology (12.3)].

7.5 Alpha-Blockers

PDE5 inhibitors, including tadalafil, and alpha-adrenergic blocking agents are both vasodilators with blood-pressure-lowering effects. In patients who are taking alpha1blockers, concomitant administration of tadalafil may lead to symptomatic hypotension in some patients. Therefore, the combination of OPSYNVI and doxazosin is not recommended [see Warnings and Precautions (5.3)and Clinical Pharmacology (12.2)].

7.6 Antihypertensives

PDE5 inhibitors, including tadalafil, are mild systemic vasodilators. Clinical pharmacology studies were conducted to assess the effect of tadalafil on the potentiation of the blood–pressure–lowering effects of selected antihypertensive medications (amlodipine, angiotensin II receptor blockers, bendroflumethiazide, enalapril, and metoprolol). Small reductions in blood pressure occurred following coadministration of tadalafil with these agents compared with placebo [see Clinical Pharmacology (12.2)].

7.7 Alcohol

Both alcohol and tadalafil, a PDE5 inhibitor, act as mild vasodilators. When mild vasodilators are taken in combination, blood-pressure–lowering effects of each individual compound may be increased. Substantial consumption of alcohol (e.g., 5 units or greater) in combination with OPSYNVI can increase the potential for orthostatic signs and symptoms, including increase in heart rate, decrease in standing blood pressure, dizziness, and headache. Tadalafil (10 mg or 20 mg) did not affect alcohol plasma concentrations and alcohol did not affect tadalafil plasma concentrations [see Clinical Pharmacology (12.2)].

8 USE IN SPECIFIC POPULATIONS

8.1 Pregnancy

Risk Summary

Based on data from animal reproduction studies, OPSYNVI is contraindicated during pregnancy. Macitentan, a component of OPSYNVI, may cause embryo-fetal toxicity, including birth defects and fetal death, when administered to a pregnant female. Available data from postmarketing reports and published literature over decades of use with ERAs in the same class as OPSYNVI have not identified an increased risk of major birth defects; however, these data are limited. Methodological limitations of these postmarketing reports and published literature include lack of a control group; limited information regarding dose, duration, and timing of drug exposure; and missing data. These limitations preclude establishing a reliable estimate of the risk of adverse fetal and neonatal outcomes with maternal ERA use. Macitentan was teratogenic in rabbits and rats at all doses tested.

Available data from a randomized controlled trial, observational studies, and case series with tadalafil use in pregnant women have not identified a drug-associated risk of major birth defects, miscarriage, or adverse maternal or fetal outcomes. In tadalafil animal reproduction studies, no adverse developmental effects were observed with oral administration of tadalafil to pregnant rats and mice during organogenesis at exposures 7 times the maximum recommended human dose (MRHD) of 40 mg/day (see Data) .

There are risks to the mother and the fetus associated with PAH in pregnancy (see Clinical Considerations) . If this drug is used during pregnancy, or if the patient becomes pregnant while taking this drug, advise pregnant women of the potential risk to a fetus [see Contraindications (4.1)and Warnings and Precautions (5.1)].

The background risk of major birth defects and miscarriage for the indicated population is unknown. All pregnancies have a background risk of birth defect, loss, or other adverse outcomes. In the U.S. general population, the estimated background risk of major birth defects and miscarriage in clinically recognized pregnancies is 2–4% and 15–20%, respectively.

Clinical Considerations

Disease-associated Maternal and/or Embryo/Fetal Risk

In patients with PAH, pregnancy is associated with an increased rate of maternal and fetal morbidity and mortality, including heart failure, stroke, spontaneous abortion, intrauterine growth restriction, premature labor, and preterm birth.

Data

Animal Data

Macitentan

In both rabbits and rats, there were cardiovascular and mandibular arch fusion abnormalities. Administration of macitentan to female rats from late pregnancy through lactation caused reduced pup survival and impairment of the male fertility of the offspring at all dose levels tested.

Tadalafil

Tadalafil and/or its metabolites cross the placenta, resulting in fetal exposure in rats.

Animal reproduction studies showed no evidence of teratogenicity, embryotoxicity, or fetotoxicity when tadalafil was given to pregnant rats or mice at unbound tadalafil exposures up to 7 times the exposure at the maximum recommended human dose (MRHD) of 40 mg/day during organogenesis based on AUC. In one of two perinatal/postnatal developmental studies in rats, a reduction of postnatal pup survival was observed at dose levels of 60, 200 and 1000 mg/kg. The no-observed-effect-level (NOEL) for developmental toxicity was 30 mg/kg, which provided maternal exposure to unbound tadalafil concentrations approximately 5 times the exposure at the MRHD based on AUC. Signs of maternal toxicity occurred at doses greater than 200 mg/kg/day, which produced AUCs greater than 8 times the exposure at the MRHD. Surviving offspring had normal development and reproductive performance.

8.2 Lactation

Risk Summary

There are no data on the presence of tadalafil, macitentan, and/or their metabolites in human milk, the effects on the breastfed infant, or the effect on milk production. Tadalafil and/or its metabolites are present in the milk of lactating rats (see Data) . When a drug is present in animal milk, it is likely that the drug will be present in human milk. Because of the potential for serious adverse reactions in breastfed infants from OPSYNVI, advise women not to breastfeed during treatment with OPSYNVI.

Data

Tadalafil and/or its metabolites are present in the milk of lactating rats at concentrations approximately 2.4-times that found in the plasma.

8.3 Females and Males of Reproductive Potential

Based on data from animal reproductive toxicity studies, OPSYNVI can cause fetal harm, including birth defects and fetal death, when administered to a pregnant patient and is contraindicated during pregnancy [see Contraindications (4.1), and Use in Specific Populations (8.1)].

Pregnancy Testing

Verify that patients who can become pregnant are not pregnant prior to initiating OPSYNVI. The patient should contact their physician immediately for pregnancy testing if onset of menses is delayed or pregnancy is suspected. If the pregnancy test is positive, the physician and patient should discuss the risks to the pregnancy, and the fetus .

Contraception

Patients who can become pregnant who are using OPSYNVI should use an effective method of contraception prior to initiation of treatment, during treatment, and for one month after discontinuation of treatment with OPSYNVI to prevent pregnancy [see Warnings and Precautions (5.1)] .

Infertility

Males

Macitentan

Based on findings in animals, macitentan may impair fertility in males of reproductive potential. It is not known whether effects on fertility would be reversible [see Warnings and Precautions (5.10), Clinical Pharmacology (12.2), and Nonclinical Toxicology (13.1)].

Tadalafil

Based on the data from 3 studies in adult males, tadalafil decreased sperm concentrations in the study of 10 mg tadalafil for 6 months and the study of 20 mg tadalafil for 9 months. This effect was not seen in the study of 20 mg tadalafil taken for 6 months. There was no adverse effect of tadalafil 10 mg or 20 mg on mean concentrations of testosterone, luteinizing hormone or follicle stimulating hormone. The clinical significance of the decreased sperm concentrations in the two studies is unknown. There have been no studies evaluating the effect of tadalafil on fertility in men or women [see Clinical Pharmacology (12.2)and Nonclinical Toxicology (13.1)] .

8.4 Pediatric Use

The safety and efficacy of OPSYNVI in children has not been established.

8.5 Geriatric Use

Of the total number of subjects in the clinical study of OPSYNVI for PAH, 20% were 65 and over. No overall differences in safety or effectiveness were observed between these subjects and younger subjects.

8.6 Renal Impairment

The use of OPSYNVI is not recommended in patients undergoing dialysis. Avoid use of OPSYNVI in patients with severe renal impairment (creatinine clearance 15–29 mL/min) because of increased tadalafil exposure (AUC), lack of clinical experience and the lack of ability to influence clearance by dialysis. For patients with mild (creatinine clearance 51–80 mL/min) to moderate (creatinine clearance 30–50 mL/min) renal impairment, the recommended dose should be consistent with the adult dosing [see Dosage and Administration (2.1)and Clinical Pharmacology (12.3)].

8.7 Hepatic Impairment

OPSYNVI was not studied in severe hepatic impairment patients defined as a Model for End-Stage Liver Disease score ≥19. OPSYNVI must not be initiated in patients with severe hepatic impairment, or clinically significant elevated hepatic aminotransferases (greater than 3 times the Upper Limit of Normal at baseline (> 3 × ULN). For patients with mild to moderate hepatic impairment (Child Pugh Class A or B) the recommended dose should be consistent with the adult dosing see Dosage and Administration (2.1)[see Warnings and Precautions (5.2)and Clinical Pharmacology (12.3)].

10 OVERDOSAGE

In the event of an overdose, standard supportive measures should be taken, as required. Dialysis is unlikely to be effective because macitentan is highly protein-bound.

Macitentan

Macitentan has been administered as a single dose of up to and including 600 mg to healthy subjects (60 times the approved dosage). Adverse reactions of headache, nausea and vomiting were observed.

Tadalafil

Single doses of tadalafil up to 500 mg have been given to healthy male subjects, and multiple daily doses up to 100 mg have been given to male patients with erectile dysfunction. Adverse reactions were similar to those seen at lower doses. Doses greater than 40 mg have not been studied in patients with PAH. Hemodialysis contributes negligibly to tadalafil elimination.

11 DESCRIPTION

OPSYNVI® is a single tablet combination containing two oral components used to treat pulmonary arterial hypertension: macitentan, an endothelin receptor antagonist (ERA), and tadalafil, a phosphodiesterase 5 (PDE5) inhibitor.

Macitentan

Macitentan is an endothelin receptor antagonist. The chemical name of macitentan is N-[5-(4-Bromophenyl)-6-[2-[(5-bromo-2-pyrimidinyl)oxy]ethoxy]-4- pyrimidinyl]-N'-propylsulfamide. It has a molecular formula of C19H20Br2N6O4S and a molecular weight of 588.27. Macitentan is achiral and has the following structural formula:

Macitentan is a crystalline powder that is insoluble in water. In the solid state macitentan is very stable, is not hygroscopic, and is not light sensitive.

Tadalafil

Tadalafil, an oral treatment for pulmonary arterial hypertension, is a selective inhibitor of cyclic guanosine monophosphate (cGMP)–specific phosphodiesterase type 5 (PDE5). Tadalafil has the empirical formula C22H19N3O4 representing a molecular weight of 389.41. The structural formula is:

The chemical designation is pyrazino[1´,2´:1,6]pyrido[3,4–b]indole-1,4-dione, 6-(1,3- benzodioxol-5-yl)-2,3,6,7,12,12a-hexahydro-2-methyl-, (6R,12aR)-. It is a crystalline solid that is practically insoluble in water and very slightly soluble in ethanol.

OPSYNVI

OPSYNVI is available as 10 mg/20 mg macitentan/tadalafil and 10 mg/40 mg macitentan/tadalafil film-coated tablets for oral administration.

Each OPSYNVI core tablet contains the following inactive ingredients: Hydroxypropyl cellulose, hydroxypropyl cellulose (low-substituted), lactose monohydrate, magnesium stearate, microcrystalline cellulose, polysorbate 80, povidone, sodium starch glycolate, sodium lauryl sulfate.

OPSYNVI 10 mg/20 mg tablets are film-coated with a coating material containing hydroxypropyl methylcellulose, iron oxide red, iron oxide yellow, lactose monohydrate, talc, titanium dioxide, and triacetin.

OPSYNVI 10 mg/40 mg tablets are film-coated with a coating material containing hydroxypropyl methylcellulose, lactose monohydrate, talc, titanium dioxide, and triacetin.

12 CLINICAL PHARMACOLOGY

12.1 Mechanism of Action

Macitentan

Endothelin (ET)-1 and its receptors (ETA and ETB) mediate a variety of deleterious effects, such as vasoconstriction, fibrosis, proliferation, hypertrophy, and inflammation. In disease conditions such as PAH, the local ET system is upregulated and is involved in vascular hypertrophy and in organ damage.

Macitentan is an endothelin receptor antagonist that inhibits the binding of ET-1 to both ETA and ETB receptors. Macitentan displays high affinity and sustained occupancy of the ET receptors in human pulmonary arterial smooth muscle cells. One of the metabolites of macitentan is also pharmacologically active at the ET receptors and is estimated to be about 20% as potent as the parent drug in vitro. The clinical impact of dual endothelin blockage is unknown.

Tadalafil

Tadalafil is an inhibitor of phosphodiesterase type 5 (PDE5), the enzyme responsible for the degradation of cyclic guanosine monophosphate (cGMP). PAH is associated with impaired release of nitric oxide by the vascular endothelium and consequent reduction of cGMP concentrations in the pulmonary vascular smooth muscle. PDE5 is the predominant phosphodiesterase in the pulmonary vasculature. Inhibition of PDE5 by tadalafil increases the concentrations of cGMP resulting in relaxation of pulmonary vascular smooth muscle cells and vasodilation of the pulmonary vascular bed.

Studies in vitrohave shown that tadalafil is a selective inhibitor of PDE5. PDE5 is an enzyme found in corpus cavernosum, vascular smooth muscle, visceral smooth muscle, skeletal muscle, platelets, kidney, lung, and cerebellum. The effect of tadalafil is more potent on PDE5 than on other phosphodiesterases. Tadalafil is > 10,000-fold more potent for PDE5 than for PDE1, PDE2, PDE4 and PDE7, enzymes which are found in the heart, brain, blood vessels, liver, and other organs. Tadalafil is > 10,000-fold more potent for PDE5 than for PDE3, an enzyme found in the heart and blood vessels. This selectivity for PDE5 over PDE3 is important because PDE3 is an enzyme involved in cardiac contractility. Additionally, tadalafil is approximately 700-fold more potent for PDE5 than for PDE6, an enzyme which is found in the retina and is responsible for phototransduction. Tadalafil is also > 9,000-fold more potent for PDE5 than for PDE8, PDE9 and PDE10.

12.2 Pharmacodynamics

Pharmacodynamic studies with OPSYNVI have not been conducted. As OPSYNVI contains macitentan and tadalafil, the pharmacodynamic effects for each component should be considered.

Pulmonary Hemodynamics of Macitentan

The SERAPHIN clinical efficacy study in patients with PAH assessed hemodynamic parameters in a subset of patients after 6 months of treatment. Patients treated with macitentan 10 mg (N=57) achieved a median reduction of 37% (95% CI 22–49) in pulmonary vascular resistance and an increase of 0.6 L/min/m^2 (95% CI 0.3–0.9) in cardiac index compared to placebo (N=67).

Effects on Cardiac Electrophysiology

Macitentan

In a randomized, placebo-controlled four-way crossover study with a positive control in healthy subjects, repeated doses of macitentan 10 and 30 mg (3 times the recommended dosage) had no significant effect on the QTc interval.

Tadalafil

In a randomized, placebo-controlled four-way crossover study with a positive control in healthy subjects, a single dose of 100 mg tadalafil (2.5 times the recommended dosage) had no significant effect on the QTc interval.

Effects on Blood Pressure When Administered with Nitrates

In clinical pharmacology studies, tadalafil (5 to 20 mg) was shown to potentiate the hypotensive effect of nitrates. Do not use OPSYNVI in patients taking any form of nitrates [see Contraindications (4.3)].

A double–blind, placebo–controlled, crossover study in 150 male subjects at least 40 years of age (including subjects with diabetes mellitus and/or controlled hypertension) assessed the interaction between nitroglycerin and tadalafil. Subjects received daily doses of tadalafil 20 mg or matching placebo for 7 days and then were given a single dose of 0.4 mg sublingual nitroglycerin (NTG) at pre–specified timepoints following their last dose of tadalafil (2, 4, 8, 24, 48, 72, and 96 hours after tadalafil). A significant interaction between tadalafil and NTG was observed at each timepoint up to and including 24 hours. At 48 hours, by most hemodynamic measures, the interaction between tadalafil and NTG was not observed, although a few more tadalafil subjects compared to placebo experienced greater blood-pressure-lowering effects at this timepoint. After 48 hours, the interaction was not detectable [see Contraindications (4.3)].

Effects on Vision

Single oral doses of PDE inhibitors have demonstrated transient dose-related impairment of color discrimination (blue/green), using the Farnsworth–Munsell 100–hue test, with peak effects near the time of peak plasma levels. This finding is consistent with the inhibition of PDE6, which is involved in phototransduction in the retina. In a study to assess the effects of a single dose of tadalafil 40 mg on vision (N=59), no effects were observed on visual acuity, intraocular pressure, or pupillometry. Across all clinical studies with tadalafil, reports of changes in color vision were rare (<0.1% of patients).

Dose-Response Relationship

Dose-response relationships, between 20 mg and 40 mg of tadalafil, were not observed for 6-minute walk distance or pulmonary vascular resistance (PVR) in subjects with PAH in the placebo-controlled study. Median change from baseline in 6-minute walk distance was 32 meters and 35 meters at 16 weeks in subjects receiving 20 mg and 40 mg daily, respectively. Mean change from baseline PVR was -254 dynes*sec*cm and -209 dynes*sec*cm at 16 weeks in patients receiving 20 mg and 40 mg daily, respectively.

12.3 Pharmacokinetics

Macitentan

The pharmacokinetics of macitentan and its active metabolite have been studied primarily in healthy subjects. The pharmacokinetics of macitentan are dose proportional over a range from 1 mg to 30 mg after once daily administration.

A cross study comparison shows that the exposures to macitentan and its active metabolite in patients with PAH are similar to those observed in healthy subjects.

Tadalafil

Over a dose range of 2.5 to 20 mg, tadalafil exposure (AUC) increases proportionally with dose in healthy subjects. In PAH patients administered between 20 and 40 mg of tadalafil, an approximately 50% greater AUC was observed indicating a less than proportional increase in exposure over the entire dose range of 2.5 to 40 mg.

During tadalafil 20 and 40 mg once daily dosing, steady-state plasma concentrations were attained within 5 days, and exposure was approximately 30% higher than after a single dose.

Absorption

Macitentan

After a single oral administration of OPSYNVI, the maximum plasma concentration of macitentan is achieved in about 10 hours. The absolute bioavailability after oral administration is not known. In a study in healthy subjects, the exposure to macitentan and its active metabolite were unchanged after a high fat breakfast. OPSYNVI may therefore be taken with or without food.

Tadalafil

After a single oral-dose administration of OPSYNVI, the maximum observed plasma concentration (Cmax) of tadalafil is achieved in about 3 hours. Absolute bioavailability of tadalafil following oral dosing has not been determined. Food intake does not significantly alter the rate and extent of absorption of tadalafil and OPSYNVI may be taken with or without food.

Distribution

Macitentan

Macitentan and its active metabolite are highly bound to plasma proteins (>99%), primarily to albumin and to a lesser extent to alpha-1-acid glycoprotein. The apparent volumes of distribution (Vss/F) of macitentan and its active metabolite were about 50 L and 40 L respectively in healthy subjects.

Tadalafil

The mean apparent volume of distribution following oral administration is approximately 77 L, indicating that tadalafil is distributed into tissues. At therapeutic concentrations, 94% of tadalafil in plasma is bound to proteins.

Metabolism

Macitentan

Following oral administration, the apparent elimination half-lives of macitentan and its active metabolite are approximately 16 and 48 hours, respectively. Macitentan is metabolized primarily by oxidative depropylation of the sulfamide to form the pharmacologically active metabolite. This reaction is dependent on the cytochrome P450 (CYP) system, mainly CYP3A4 with minor contributions of CYP2C8, CYP2C9, and CYP2C19. At steady state in PAH patients, the systemic exposure to the active metabolite is 3-times the exposure to macitentan and is expected to contribute approximately 40% of the total pharmacologic activity.

Tadalafil

Tadalafil is predominantly metabolized by CYP3A to a catechol metabolite. The catechol metabolite undergoes extensive methylation and glucuronidation to form the methylcatechol and methylcatechol glucuronide conjugate, respectively. The major circulating metabolite is the methylcatechol glucuronide. Methylcatechol concentrations are less than 10% of glucuronide concentrations. In vitrodata suggests that metabolites are not expected to be pharmacologically active at observed metabolite concentrations.

Elimination

Macitentan

In a study in healthy subjects with radiolabeled macitentan, approximately 50% of radioactive drug material was eliminated in urine but none was in the form of unchanged drug or the active metabolite. About 24% of the radioactive drug material was recovered from feces.

Tadalafil

Following 40 mg, the mean oral clearance for tadalafil is 3.4 L/hr and the mean effective half-life is 11 hours in healthy subjects. In patients with pulmonary hypertension not receiving concomitant bosentan, the mean oral clearance for tadalafil is 1.6 L/hr. Tadalafil is excreted predominantly as metabolites, mainly in the feces (approximately 61% of the dose) and to a lesser extent in the urine (approximately 36% of the dose).

Population Pharmacokinetics

Tadalafil

In patients with pulmonary hypertension not receiving concomitant bosentan, the average tadalafil exposure at steady-state following 40 mg was 26% higher when compared to those of healthy volunteers. The results suggest a lower clearance of tadalafil in patients with pulmonary hypertension compared to healthy volunteers.

Specific Populations

Renal Impairment

Macitentan

Exposure to macitentan and its active metabolite in patients with severe renal impairment (creatinine clearance 15–29 mL/min) compared to healthy subjects was increased by 30% and 60%, respectively. This increase is not considered clinically relevant.

Tadalafil

In clinical pharmacology studies using single-dose tadalafil (5 to 10 mg), tadalafil exposure (AUC) doubled in subjects with mild (creatinine clearance 51 to 80 mL/min) or moderate (creatinine clearance 30 to 50 mL/min) renal impairment. In subjects with end-stage renal disease on hemodialysis, Cmax doubled and AUC was 2.7 to 4.1 times as high following single-dose administration of 10 or 20 mg tadalafil, respectively. Exposure to total methylcatechol (unconjugated plus glucuronide) was 2 to 4-times as high in subjects with renal impairment, compared to those with normal renal function. Hemodialysis (performed between 24-and 30-hours post-dose) contributed negligibly to tadalafil or metabolite elimination.

Hepatic Impairment

Macitentan

Exposure to macitentan was decreased by 21%, 34%, and 6% and exposure to the active metabolite was decreased by 20%, 25%, and 25% in subjects with mild, moderate, or severe hepatic impairment (Child-Pugh Class A, B, and C), respectively. This decrease is not considered clinically relevant.

Tadalafil

In clinical pharmacology studies, tadalafil exposure (AUC) in subjects with mild or moderate hepatic impairment (Child-Pugh Class A or B) was similar to exposure in healthy subjects when a dose of 10 mg was administered. There are no available data for doses higher than 10 mg of tadalafil in patients with hepatic impairment. Insufficient data are available for subjects with severe hepatic impairment (Child-Pugh Class C) .

Geriatric Patients

Macitentan

There are no clinically relevant effects of age on the pharmacokinetics of macitentan and its active metabolite.

Tadalafil

In healthy male elderly subjects (65 years or over) after a 10 mg dose, a lower oral clearance of tadalafil, resulting in 25% higher exposure (AUC) with no effect on Cmax was observed relative to that in healthy subjects 19 to 45 years of age.

Patients with Diabetes Mellitus

Tadalafil

In male patients with diabetes mellitus after a 10 mg tadalafil dose, exposure (AUC) was reduced approximately 19% and Cmax was 5% lower than that observed in healthy subjects. No dose adjustment is warranted.

Race and gender

There are no clinically relevant effects of race or gender on macitentan, its active metabolite, or tadalafil.

Drug Interactions

No clinical study evaluating drug interactions has been performed using OPSYNVI. Interactions that have been identified in studies with individual components of OPSYNVI (macitentan or tadalafil) determine the interactions that may occur with OPSYNVI. Co-administration of macitentan (10 mg once daily) and tadalafil (40 mg once daily) had no clinically relevant effect on the pharmacokinetics of either macitentan or tadalafil.

Macitentan

The metabolism of macitentan to its active metabolite is catalyzed mainly by CYP3A4, with minor contributions from CYP2C8, CYP2C9, and CYP2C19.

Macitentan and its active metabolite do not have relevant inhibitory or inducing effects on CYP enzymes.

Macitentan and its active metabolite are not substrates of the multi-drug resistance protein (P-gp, MDR-1) or organic anion transporting polypeptides (OATP1B1 and OATP1B3).

Macitentan and its active metabolite are not inhibitors of hepatic or renal drug transporters at clinically relevant concentrations.

Tadalafil

Tadalafil is a substrate of and predominantly metabolized by CYP3A.

Effects of other drugs on macitentan or tadalafil

Strong CYP3A4 inducers or inhibitors

Macitentan

Concomitant treatment with rifampicin 600 mg daily, a potent inducer of CYP3A4, reduced the steady-state exposure to macitentan by 79% but did not affect the exposure to the active metabolite [see Drug Interactions (7.2)].

Concomitant use of strong CYP3A4 inhibitors like ketoconazole approximately double macitentan exposure. Effects of other strong CYP3A4 inhibitors such as ritonavir on macitentan were not studied but are likely to result in an increase in macitentan exposure at steady state similar to that seen with ketoconazole [see Drug Interactions (7.3)] .

A moderate dual inhibitor of CYP3A4 and CYP2C9 such as fluconazole (400 mg once daily) is predicted to increase macitentan exposure approximately 4-fold without relevant effect on the exposure to its active metabolite [see Drug Interactions (7.4)] .

Tadalafil

Rifampin (600 mg daily), a CYP3A inducer, reduced tadalafil 10 mg single-dose exposure (AUC) by 88% and Cmax by 46%, relative to the values for tadalafil 10 mg alone [see Drug Interactions (7.2)] .

Bosentan, a substrate of CYP2C9 and CYP3A and a moderate inducer of CYP3A, CYP2C9 and possibly CYP2C19, reduced tadalafil systemic exposure following multiple-dose coadministration. Although specific interactions have not been studied, other CYP3A inducers, such as carbamazepine, phenytoin, and phenobarbital, would likely decrease tadalafil exposure [see Drug Interactions (7.2)].

Ketoconazole increased tadalafil exposure relative to the values for tadalafil alone. Although specific interactions have not been studied, other CYP3A inhibitors, such as erythromycin, itraconazole, and grapefruit juice, would likely increase tadalafil exposure [see Drug Interactions (7.3)].

Ritonavir increased tadalafil 20-mg single-dose exposure relative to the values for tadalafil alone. Ritonavir inhibits and induces CYP3A, the enzyme involved in the metabolism of tadalafil, in a time-dependent manner. The initial inhibitory effect of ritonavir on CYP3A may be mitigated by a more slowly evolving induction effect so that after about 1 week of ritonavir twice daily, the exposure of tadalafil is similar in the presence of and absence of ritonavir [see Drug Interactions (7.3)] .

Effects of macitentan or tadalafil on other medicinal products

Macitentan

Macitentan once daily dosing did not alter the exposure to R- and S-warfarin or their effect on international normalized ratio (INR).

At steady state, the exposure to sildenafil 20 mg t.i.d. increased by 15% during concomitant administration of macitentan 10 mg once daily. This change is not considered clinically relevant. Macitentan 10 mg once daily did not affect the pharmacokinetics of an oral contraceptive (norethisterone 1 mg and ethinyl estradiol 35 µg).

Macitentan 10 mg once daily did not affect the pharmacokinetics of concomitant use of a BCRP substrate drug (riociguat 1 mg and rosuvastatin 10 mg).

Tadalafil

Tadalafil is not expected to cause clinically significant inhibition or induction of the clearance of drugs metabolized by cytochrome P450 (CYP) isoforms.

Exposure changes of drugs following co-administration with tadalafil are shown in Figure 1.

Figure 1: Impact of Tadalafil on the Pharmacokinetics of Other Drugs

aA small augmentation (increase of 3 beats per minute) in heart rate was observed with theophylline.
bTadalafil (40 mg qd) had no clinically significant effect on exposure (AUC and C) of bosentan
metabolites.
c95% CI

13 NONCLINICAL TOXICOLOGY

13.1 Carcinogenesis, Mutagenesis, Impairment of Fertility

Carcinogenesis

Macitentan

Carcinogenicity studies of 2 years' duration did not reveal any carcinogenic potential at exposures 75-fold and 140-fold the human exposure (based on AUC) in male and female mice, respectively, and 8.3-and 42-fold in male and female rats, respectively.

Tadalafil

Tadalafil was not carcinogenic to rats or mice when administered daily for 2 years at doses up to 400 mg/kg/day. Systemic drug exposures, as measured by AUC of unbound tadalafil, were approximately 5-fold for mice, and 7-and 14-fold for male and female rats, respectively, the exposures at the maximum recommended human dose (MRHD) of 40 mg.

Mutagenesis

Macitentan

Macitentan was not genotoxic in a standard battery of in vitroand in vivoassays that included a bacterial reverse mutation assay, an assay for gene mutations in mouse lymphoma cells, a chromosome aberration test in human lymphocytes, and an in vivomicronucleus test in rats.

Tadalafil

Tadalafil was not mutagenic in the in vitrobacterial Ames assays or the forward mutation test in mouse lymphoma cells. Tadalafil was not clastogenic in the in vitrochromosomal aberration test in human lymphocytes or the in vivorat micronucleus assays.

Impairment of Fertility

Macitentan

Treatment of juvenile rats from postnatal Day 4 to Day 114 led to reduced body weight gain and testicular tubular atrophy at exposures 7-fold the human exposure. Fertility was not affected.

Reversible testicular tubular dilatation was observed in chronic toxicity studies at exposures greater than 7-fold and 23-fold the human exposure in rats and dogs, respectively. After 2 years of treatment, tubular atrophy was seen in rats at 4-fold the human exposure. Macitentan did not affect male or female fertility at exposures ranging from 19-to 44-fold the human exposure, respectively, and had no effect on sperm count, motility, and morphology in male rats. No testicular findings were noted in mice after treatment up to 2 years.

Tadalafil

There were no effects on fertility, reproductive performance or reproductive organ morphology in male or female rats given oral doses of tadalafil up to 400 mg/kg/day, a dose producing AUCs for unbound tadalafil of 6-fold for males or 17-fold for females the exposures at the MRHD of 40 mg. In beagle dogs given tadalafil daily for 3 to 12 months, there was treatment-related non-reversible degeneration and atrophy of the seminiferous tubular epithelium in the testes in 20–100% of the dogs that resulted in a decrease in spermatogenesis in 40–75% of the dogs at doses of ≥10 mg/kg/day. Systemic exposure (based on AUC) at no-observed-adverse-effect-level (NOAEL) (10 mg/kg/day) for unbound tadalafil was similar to that expected in humans at the MRHD of 40 mg.

There were no treatment-related testicular findings in rats or mice treated with doses up to 400 mg/kg/day for 2 years.

13.2 Animal Toxicology and/or Pharmacology

Macitentan

In dogs, macitentan decreased blood pressure at exposures similar to the therapeutic human exposure. Intimal thickening of coronary arteries was observed at 17-fold the human exposure after 4 to 39 weeks of treatment. Due to the species-specific sensitivity and the safety margin, this finding is considered not relevant for humans.

There were no adverse liver findings in long-term studies conducted in mice, rats and dogs at exposures of 12-to 116-fold the human exposure.

Tadalafil

Animal studies showed vascular inflammation in tadalafil-treated mice, rats, and dogs. In mice and rats, lymphoid necrosis and hemorrhage were seen in the spleen, thymus, and mesenteric lymph nodes at unbound tadalafil exposure of 1-to 17-fold the human exposure (AUCs) at the MRHD of 40 mg. In dogs, an increased incidence of disseminated arteritis was observed in 1-and 6-month studies at unbound tadalafil exposure of 0.5-to 38-fold the human exposure (AUC) at the MRHD of 40 mg. In a 12-month dog study, no disseminated arteritis was observed, but 2 dogs exhibited marked decreases in white blood cells (neutrophils) and moderate decreases in platelets with inflammatory signs at unbound tadalafil exposures of approximately 4-to 10-fold the human exposure at the MRHD of 40 mg. The abnormal blood-cell findings were reversible within 2 weeks upon removal of the drug.

14 CLINICAL STUDIES

14.1 Pulmonary Arterial Hypertension

OPSYNVI

OPSYNVI was demonstrated to reduce pulmonary vascular resistance (PVR) in a multi-national, multi-center, double-blind, adaptive, randomized, active-controlled, parallel-group study [NCT03904693 (A DUE)] in 187 patients with PAH (WHO FC II–III). The study was designed to compare the efficacy and safety of OPSYNVI to each monotherapy macitentan or tadalafil. Patients with PVR of at least 240 dyn∙s/cm^5 were randomized to receive OPSYNVI (n=108), 10 mg macitentan monotherapy (n=35) or 40 mg tadalafil monotherapy (n=44), once daily.

Patients who received treatment during the double-blind treatment period (n=186) were either treatment-naïve (53%) or on an ERA (17%) or a PDE5 inhibitor (30%). Patients enrolled had idiopathic PAH (51%), heritable PAH (5%), PAH associated with connective tissue disease (35%), or PAH associated with congenital heart disease (3%). The mean age was 50 years (range 18–80), 20% of patients were ≥65 years of age, 22% were male and 62% were white. At the time of enrollment, 51% of patients were WHO FC II and 49% were WHO FC III.

Patients who were not on a therapeutic PDE5 inhibitor dose at baseline received a 1-week titration period of macitentan 10 mg and tadalafil 20 mg.

The primary endpoint of the study was change from baseline in PVR (expressed as the ratio of geometric means of end of double-blind treatment to baseline) vs the individual component monotherapies after 16 weeks.

Hemodynamic

OPSYNVI demonstrated greater reduction in PVR after 16 weeks. Treatment with OPSYNVI resulted in a statistically significant treatment effect of 0.71 (95% CL 0.61, 0.82, p < 0.0001) representing a 29% reduction in PVR as compared to macitentan, and of 0.72 (95% CLs 0.64, 0.80, p < 0.0001) representing a 28% reduction in PVR as compared to tadalafil (Table 4).

Table 4: Change from Baseline in PVR at Week 16
 | Treatment-naïve and Prior ERA Treatment |  | Treatment-naïve and Prior PDE5 Inhibitor Treatment
 | Macitentan (n=35) | OPSYNVI (n=70) | Tadalafil (n=44) | OPSYNVI (n=86)
Baseline mean (SD) | 816 (401) | 834 (631) | 802 (552) | 885(640)
Reduction at Week 16 (dynes *sec/cm5) Mean (SD) | -162 (240) | -371 (429) | -181 (238) | -385 (396)
Geometric mean (Week 16/Baseline) | 0.77 | 0.55 | 0.78 | 0.56
Treatment effect ratios (95% CL) |  | -29% (-39%, -18%) |  | -28% (-36%, -20%)
2-sided p-value |  | <0.0001 |  | <0.0001

A consistent effect of OPSYNVI on reducing PVR was seen across subgroups of age, sex, race, geographical region, and baseline WHO FC (see Figure 2). Additionally, a consistent effect was observed in patients who were either treatment-naïve, or previously exposed to an ERA or PDE5 inhibitor.

Figure 2: Subgroup Analysis of the A DUE Study

The individual components of OPSYNVI, macitentan and tadalafil, have been approved and used independently or concomitantly in the clinical setting to effectively manage PAH. Macitentan is an endothelin receptor antagonist (ERA) indicated for the treatment of pulmonary arterial hypertension (PAH, WHO Group I) to reduce the risks of disease progression and hospitalization for PAH. Tadalafil is a phosphodiesterase 5 (PDE5) inhibitor indicated for the treatment of pulmonary arterial hypertension (PAH, WHO Group 1) to improve exercise ability.

Macitentan

The primary efficacy endpoint of the multi-center, long-term, placebo-controlled SERAPHIN study was time to the first occurrence of death, a significant morbidity event, defined as atrial septostomy, lung transplantation, initiation of intravenous or subcutaneous prostanoids, or "other worsening of PAH" during double-blind treatment plus 7 days. Other worsening was defined as all of the following: 1) a sustained ≥15% decrease from baseline in 6-minute walk distance (6MWD), 2) worsening of PAH symptoms (worsening of WHO FC), and 3) need for additional treatment for PAH. All of these other worsening events were confirmed by an independent adjudication committee, blinded to treatment allocation.

Treatment with OPSUMIT 10 mg reduced the risk of clinical worsening events and hospitalization for PAH.

Tadalafil

The primary efficacy endpoint of a randomized, 16-week placebo-controlled study was the change from baseline at week 16 in 6-minute walk distance. Treatment with tadalafil 40 mg improved exercise ability.

16 HOW SUPPLIED/STORAGE AND HANDLING

OPSYNVI® (macitentan and tadalafil) tablets, 10 mg/20 mg, are supplied as pink, oblong film-coated tablets debossed with "1020" on one side and "MT" on the other side.

OPSYNVI 10 mg/20 mg is supplied as follows:

7-count bottles with child-resistant closure NDC 66215-812-07
7-count blister NDC 66215-812-08
30-count bottle with child-resistant closure NDC 66215-812-30

OPSYNVI® (macitentan and tadalafil) tablets, 10 mg/40 mg, are supplied as white to almost-white, oblong film-coated tablets debossed with "1040" on one side and "MT" on the other side.

OPSYNVI 10 mg/40 mg is supplied as follows:

10-count blister NDC 66215-814-10
30-count bottle with child-resistant closure NDC 66215-814-30

STORAGE AND HANDLING

Store at 20ºC to 25ºC (68ºF to 77ºF); excursions are permitted between 15°C and 30°C (59°F and 86°F) [see USP Controlled Room Temperature]. Store and dispense in the original package to protect from moisture. Do not discard the desiccant.

17 PATIENT COUNSELING INFORMATION

Advise the patient to read the FDA-approved patient labeling (Medication Guide).

Embryo-Fetal Toxicity

Counsel female patients of reproductive potential about the need to use effective methods of contraception prior to initiation of treatment with OPSYNVI, during treatment, and for one month after treatment discontinuation. Females of reproductive potential should have a negative pregnancy test prior to treatment with OPSYNVI [see Contraindications (4.1), and Use in Specific Populations (8.1, 8.3)] .

Patients should be instructed to contact their physician if they suspect they may be pregnant. Patients should seek additional contraceptive advice from a gynecologist or similar expert as needed.

Educate and counsel females of reproductive potential on the use of emergency contraception in the event of unprotected sex or contraceptive failure.

Advise pre-pubertal females to report any changes in their reproductive status immediately to her prescriber.

Review the Medication Guide with female patients.

Lactation

Advise women not to breastfeed during treatment with OPSYNVI [see Use in Specific Populations (8.2)] .

Infertility

Advise males of reproductive potential that OPSYNVI may impair fertility [see Warnings and Precautions (5.10), Clinical Pharmacology (12.2), Use in Specific Populations (8.3), and Nonclinical Toxicology (13.1)].

Hepatotoxicity

Some members of this pharmacological class are hepatotoxic. Educate patients on signs of hepatotoxicity. Advise patients that they should contact their doctor if they have unexplained nausea, vomiting, right upper quadrant pain, fatigue, anorexia, jaundice, dark urine, fever, or itching.

Hemoglobin Decrease

Advise patients that they may develop anemia. Advise patients that they will have blood tests to check their red blood cells before starting OPSYNVI.

Use with Organic Nitrates or Guanylate Cyclase (GC) Stimulators

Inform patients of contraindication of OPSYNVI with any use of organic nitrates or GC stimulators.

Vision Loss

Advise patients to seek immediate medical attention in the event of a sudden loss of vision in one or both eyes while taking OPSYNVI. Such an event may be a sign of NAION. Also discuss with patients that there is an increased risk of NAION in individuals who have already experienced NAION in one eye, including whether such individuals could be adversely affected by use of vasodilators such as PDE5 inhibitors.

Hearing Loss

Advise patients to seek prompt medical attention in the event of sudden decrease or loss of hearing while taking OPSYNVI. These events may be accompanied by tinnitus and dizziness.

Fluid Retention

Educate patients on signs of fluid retention. Advise patients that they should contact their doctor if they have unusual weight increase or swelling of the ankles or legs.

Administration

Patients should be advised not to cut, crush, or chew tablets.

Manufactured for:

Actelion Pharmaceuticals US, Inc.
a Janssen Pharmaceutical Company
Titusville, NJ 08560, USA

For patent information: www.janssenpatents.com
© 2024 Actelion Pharmaceuticals US, Inc.

MEDICATION GUIDE
OPSYNVI® (op-SIN-vee)
(macitentan and tadalafil)
tablets

Read this Medication Guide for OPSYNVI before you start taking OPSYNVI and each time you get a refill. There may be new information. This Medication Guide does not take the place of talking with your healthcare provider about your medical condition or your treatment.

What is the most important information I should know about OPSYNVI?

- Serious birth defects.

OPSYNVI can cause serious birth defects if taken during pregnancy.

- Females should not be pregnant when they start taking OPSYNVI or become pregnant during treatment with OPSYNVI.
- Females who are able to get pregnant should have a negative pregnancy test before beginning treatment with OPSYNVI.
  Talk to your healthcare provider about your menstrual cycle. Your healthcare provider will decide when to do the pregnancy test and will order a pregnancy test for you depending on your menstrual cycle.
  - Females who are ableto get pregnant are females who:
    - have entered puberty, even if they have not started their menstrual period, and
    - have a uterus, and
    - have not gone through menopause. Menopause means that you have not had a menstrual period for at least 12 months for natural reasons, or that you have had your ovaries removed.
  - Females who are not ableto get pregnant are females who:
    - have not yet entered puberty, or
    - do not have a uterus, or
    - have gone through menopause. Menopause means that you have not had a menstrual period for at least 12 months for natural reasons, or that you have had your ovaries removed, or
    - are infertile for other medical reasons and this infertility is permanent and cannot be reversed.

Females who are able to get pregnant should use effective birth control before starting treatment with OPSYNVI, during treatment, and for 1 month after stopping OPSYNVI because the medicine may still be in the body.

- Talk with your healthcare provider or gynecologist (a doctor who specializes in female reproduction) to find out about options for acceptable birth control that you may use to prevent pregnancy during treatment with OPSYNVI.
- If you decide that you want to change the form of birth control that you use, talk with your healthcare provider or gynecologist to be sure that you choose another acceptable form of birth control.
- Do not have unprotected sex.Talk to your healthcare provider or pharmacist right away if you have unprotected sex or if you think your birth control has failed. Your healthcare provider may talk with you about using emergency birth control.
- Tell your healthcare provider right away if you miss a menstrual period or think you may be pregnant.

If you are the parent or caregiver of a female child who started taking OPSYNVI before reaching puberty, you should check your child regularly to see if she is developing signs of puberty. Tell your healthcare provider right away if you notice that she is developing breast buds or any pubic hair. Your healthcare provider should decide if your child has reached puberty. Your child may reach puberty before having her first menstrual period.
If you are a female who can get pregnant, you should talk to your healthcare provider to understand the benefits and risks of OPSYNVI.
See " What are the possible side effects of OPSYNVI?" for more information about side effects.

What is OPSYNVI?

- OPSYNVI is a prescription medicine that contains 2 medicines called macitentan and tadalafil. OPSYNVI is used for long-term treatment of adults with pulmonary arterial hypertension (PAH), which is high blood pressure in the arteries of your lungs.
- It is not known if OPSYNVI is safe and effective in children.

Who should not take OPSYNVI?
Do not take OPSYNVI if you:

- are pregnant, plan to become pregnant, or become pregnant during treatment with OPSYNVI. OPSYNVI can cause serious birth defects (see " What is the most important information I should know about OPSYNVI?")
- are allergic to macitentan, tadalafil, or any of the ingredients in OPSYNVI. See the end of this Medication Guide for a complete list of ingredients in OPSYNVI.
- take any medicines called nitrates
- take any medicines called guanylate cyclase (GC) stimulators

Before taking OPSYNVI, tell your healthcare provider about all of your medical conditions, including if you:

- have liver problems
- have low blood pressure
- have anemia
- have heart problems including heart attack or heart failure
- have pulmonary veno-occlusive disease (PVOD)
- have any eye problems, including NAION or an inherited eye disorder called retinitis pigmentosa
- have hearing problems such as ringing in the ears, dizziness, or loss of hearing
- have a deformed penis shape or Peyronie's disease or have blood cell problems such as sickle cell anemia, multiple myeloma, or leukemia. These conditions increase your risk of getting a prolonged erection.
- have kidney problems or get dialysis
- are pregnant or plan to become pregnant during OPSYNVI treatment. OPSYNVI can cause serious birth defects. See " What is the most important information I should know about OPSYNVI?"
- are breastfeeding or plan to breast feed. It is not known if OPSYNVI passes into your breastmilk. Do notbreastfeed during treatment with OPSYNVI.

Tell your healthcare provider about all the medicines you take, including prescription and over-the-counter medicines, vitamins, and herbal supplements.Taking OPSYNVI with other medicines may affect the way OPSYNVI and the other medicines work, and may increase your risk of side effects. Do notstart any new medicine until you check with your healthcare provider.
Especially tell your healthcare provider if you take:

- nitrate medicines
- HIV medicines
- antifungal medicines

- antiseizure medicines
- medicines used to treat infection
- erectile dysfunction medicines

- blood pressure medicines
- medicines used to treat PAH or heart problems

Ask your healthcare provider or pharmacist if you are not sure if your medicine is one that is listed above. Know the medicines you take. Keep a list and show it to your healthcare provider or pharmacist when you get a new medicine.

How should I take OPSYNVI?
OPSYNVI will be mailed to you by a specialty pharmacy. Your healthcare provider will give you complete details.

- Take OPSYNVI exactly as your healthcare provider tells you to take it. Do notstop taking OPSYNVI unless your healthcare provider tells you.
- Take OPSYNVI with or without food.
- Do notcut, crush, or chew OPSYNVI tablets.
- If you take too much OPSYNVI, call your healthcare provider or go to the nearest hospital emergency room right away.
- If you miss a dose of OPSYNVI, take it as soon as you remember that day. Take the next dose at your regular time. Do nottake 2 doses at the same time to make up for a missed dose.

What should I avoid while taking OPSYNVI?

- Do nothave more than 4 alcohol-containing drinks in a short period of time during treatment with OPSYNVI. Drinking too much alcohol can increase your chances of getting low blood pressure, increased heart rate, dizziness, and headache.

What are the possible side effects of OPSYNVI?

OPSYNVI can cause serious side effects, including:

- Serious birth defects.See " What is the most important information I should know about OPSYNVI?"
- Liver problems. OPSYNVI can cause liver problems. Your healthcare provider should do blood tests to check your liver before you start taking OPSYNVI. Tell your healthcare provider if you have any of the following symptoms of liver problems during treatment with OPSYNVI.

- nausea or vomiting
- pain in the upper right stomach
- tiredness
- loss of appetite

- yellowing of your skin or whites of your eyes
- dark urine
- fever
- itching

- Decreased blood pressure (hypotension).OPSYNVI can cause low blood pressure that lasts for a short time.
- Low red blood cell levels (anemia) can occur with OPSYNVI treatment, usually during the first weeks after starting therapy.Your healthcare provider will do blood tests to check your red blood cells before starting and as needed during treatment with OPSYNVI.
- Vision loss.OPSYNVI can cause decreased eyesight or permanent loss of vision in 1 or both eyes, which could be a sign of NAION. There is an increased risk of NAION in people who have already had NAION in 1 eye. If you notice a sudden decrease or loss of vision in 1 or both eyes, contact your healthcare provider right away.
- Hearing problems.Sudden decrease or loss of hearing, sometimes with ringing in the ears and dizziness, can happen during treatment with OPSYNVI. If you notice a sudden decrease or loss of hearing, contact your healthcare provider right away.
- Fluid retention.Fluid retention can happen within weeks after starting OPSYNVI and could lead to hospitalization. Tell your healthcare provider right away if you have any unusual weight gain, trouble breathing, or swelling of your ankles or legs. Your healthcare provider will look for the cause of any fluid retention and may stop treatment with OPSYNVI.
- Decreased sperm count.OPSYNVI can cause decreased sperm counts in males and may affect the ability to father a child. Tell your healthcare provider if being able to have children is important to you.
- Prolonged erection.Erections that last more than 4 hours, with or without pain, can happen during treatment with OPSYNVI. Painful erections (priapism) can cause permanent damage to the penis if not treated right away. Tell your healthcare provider right away if you have an erection that lasts longer than 4 hours, with or without pain.

The most common side effects of OPSYNVI include:

- too much fluid in your body (fluid retention) and swelling caused by too much fluid (edema)
- anemia
- headache, including migraine headache

These are not all the possible side effects of OPSYNVI.
Call your doctor for medical advice about side effects. You may report side effects to FDA at 1-800-FDA-1088.

How should I store OPSYNVI?

- Store OPSYNVI tablets at room temperature between 68°F to 77°F (20°C to 25°C).
- Store OPSYNVI in the package that it comes in to protect from moisture.
- OPSYNVI contains a desiccant to help keep the tablets dry. Do notdiscard or eat the desiccant.
- OPSYNVI bottles have a child-resistant cap.
- Keep OPSYNVI and all medicines out of the reach of children.

General information about the safe and effective use of OPSYNVI.
Medicines are sometimes prescribed for purposes other than those listed in a Medication Guide. Do not use OPSYNVI for a condition for which it was not prescribed. Do not give OPSYNVI to other people, even if they have the same symptoms that you have. It may harm them. You can ask your pharmacist or healthcare provider for information about OPSYNVI that is written for health professionals.

What are the ingredients in OPSYNVI?
Active ingredients:macitentan and tadalafil
Inactive ingredients: tablet core:hydroxypropyl cellulose, hydroxypropyl cellulose (low substituted), lactose monohydrate, magnesium stearate, microcrystalline cellulose, polysorbate 80, povidone, sodium starch glycolate, sodium lauryl sulfate. 10 mg/20 mg film-coating:hydroxypropyl methylcellulose, iron oxide red, iron oxide yellow, lactose monohydrate, talc, titanium dioxide, triacetin. 10 mg/40 mg film-coating:hydroxypropyl methylcellulose, lactose monohydrate, talc, titanium dioxide, triacetin.
Manufactured for:
Actelion Pharmaceuticals US, Inc.
a Janssen Pharmaceutical Company
Titusville, NJ 08560, USA
For patent information: www.janssenpatents.com
For more information, call 1-800-526-7736 (1-800-JANSSEN), or visit www.OPSYNVI.com.
© 2024 Actelion Pharmaceuticals US, Inc.

This Medication Guide has been approved by the U.S. Food and Drug Administration.

Issued: 4/2025

PRINCIPAL DISPLAY PANEL - 10 mg/20 mg Tablet Bottle Carton

NDC 66215-812-30
Rx only

Opsynvi®
(macitentan and tadalafil)
tablets

10 mg / 20 mg

Attention: Dispense the enclosed
Medication Guide to each patient.

30 film-coated tablets

PRINCIPAL DISPLAY PANEL - 10 mg/40 mg Tablet Bottle Carton

NDC 66215-814-30
Rx only

Opsynvi®
(macitentan and tadalafil)
tablets

10 mg / 40 mg

Attention: Dispense the enclosed
Medication Guide to each patient.

30 film-coated tablets